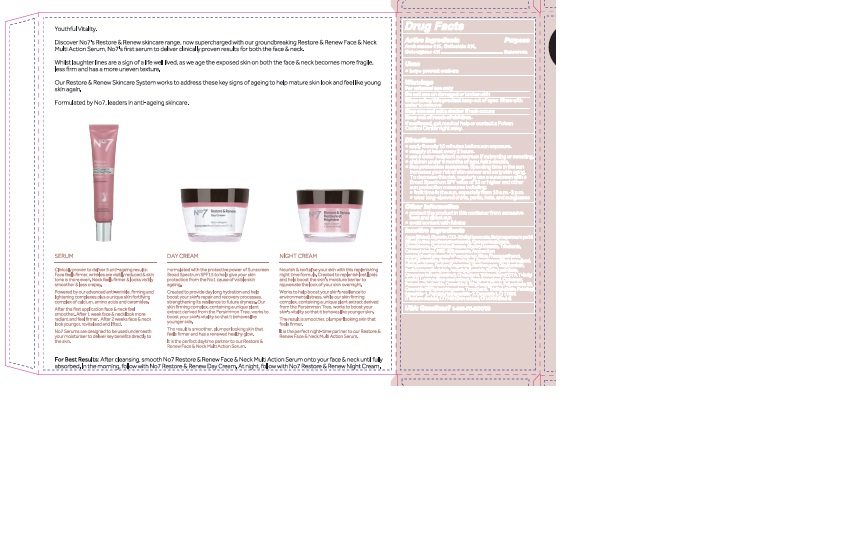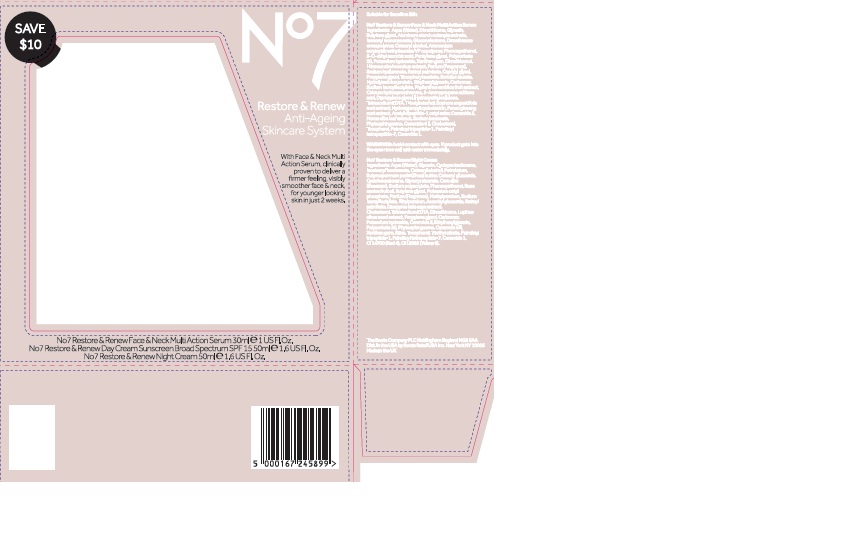 DRUG LABEL: No7 Restore and Renew Day Cream SPF 15
NDC: 11489-115 | Form: CREAM
Manufacturer: BCM Ltd
Category: otc | Type: HUMAN OTC DRUG LABEL
Date: 20170428

ACTIVE INGREDIENTS: AVOBENZONE 1.5 g/50 g; OCTOCRYLENE 2 g/50 g; OCTISALATE 1 g/50 g
INACTIVE INGREDIENTS: WATER; GLYCERIN; DIMETHICONE; ALKYL (C12-15) BENZOATE; ISOSTEARYL ISOSTEARATE; TRIBEHENIN; CYCLOMETHICONE 5; AMMONIUM ACRYLOYLDIMETHYLTAURATE/VP COPOLYMER; CYCLOMETHICONE 6; GLYCERYL STEARATE SE; PHENOXYETHANOL; CETOSTEARYL ALCOHOL; SHEA BUTTER; PEG-100 STEARATE; BUTYLENE GLYCOL; MYRISTYL MYRISTATE; ROSA CANINA FRUIT OIL; METHYLPARABEN; DIMETHICONOL (40 CST); ETHYLPARABEN; XANTHAN GUM; SODIUM LAUROYL LACTYLATE; VITAMIN A PALMITATE; ASCORBYL GLUCOSIDE; DIOSPYROS KAKI LEAF; EDETATE SODIUM; CHOLESTEROL; TERT-BUTYL ALCOHOL; LUPINUS ALBUS SEED OIL; PROPYLENE GLYCOL; POLYSORBATE 20; CARBOMER 940; POTASSIUM HYDROXIDE; ETHYLHEXYLGLYCERIN; CERAMIDE 3; CERAMIDE 6 II; TOCOPHEROL; PHYTOSPHINGOSINE; TITANIUM DIOXIDE; TRIETHYL CITRATE; PALMITOYL TETRAPEPTIDE-7; PALMITOYL TRIPEPTIDE-1; CERAMIDE 1; FD&C RED NO. 4

No7 Restore and Renew Day Cream Sunscreen Broad Spectrum SPF15

Carton Active Ingredients Section

Active ingredients

Avobenzone 3%

Octisalate 2%

Octocrylene 4%

Uses

Uses - helps prevent sunburn

Warnings

For external use only

Do not use on damaged or broken skin

When using this product keep out of eyes. Rinse with water to remove.

Ask a doctor

Stop use and ask a doctor if rash occurs

Keep out of reach of children

If swallowed, get medical help or contact a Poison Control Center right away

Directions

Apply liberally 15 minutes before sun exposure

reapply at least every 2 hours

use a water resistant sunscreen if swimming or sweating

children under 6 months of age: Ask a doctor

Sun Protection Measures. Spending time in the sun increases your risk of skin cancer and early skin aging.

To decrease this risk, regularly use a sunscreen with a Broad Spectrum SPF value of 15 or higher and other sun protection measures including:

Limit time in the sun, especially from 10 a.m - 2 p.m.

wear long-sleeved shirts,pants,hats and sunglasses.

Storage

Other information

Protect the product in this container from excessive heat and direct sun

Avoid contact with fabrics

Inactive ingredients

Aqua(Water), Glycerin, C12-15 alkyl bezoate, Butyrospermum parkii (Shea) butter, Isostearyl isostearate, Cyclopentasiloxane, Dimethicone, Cyclohexasiloxane, Glyeryl stearate, Tribehenin, Cetearyl alcohol, PEG-100 stearate, Ammonium acryloyldimethyltaurate/VP copolymer, Silica, Phenoxyethanol, Myristyl myristate, Rosa canina fruit oil, Dimethiconol, Butylene glycol, Methylparaben, Parfum(Fragrance), Xanthan gum, Ethylparaben, Sodium lauroyl lactylate, Ascorbyl glucoside, Retinyl palmitate, Diospyros kaki calyx extract, Cholesterol, Tetrasodium EDTA, T-butyl alcohol, Lupinus albus seed extract, Propylene glycol, Carbomer, Potassium hydroxide, Ceramide 3, Ethylhexylglycerin, Polysorbate 20, Ceramide 6 ll, Phytosphingosine, Tocopherol, Triethyl citrate, Palmitoyl tripeptide-1, Palmitoyl tetrapeptide-7, Ceramide 1, CI77891(Titanium dioxide) CI 77491(Iron oxides), CI14700(Red 4)

PATIENT COUNSELING INFORMATION

The Boots Company PLC Nottingham England NG2 3AA

Dist. by Boots Retail USA Inc. New York NY 10005

Made in the UK

www.boots.com

Description

No7 Restore and Renew Anti-Ageing Skincare System

With Face and Neck Multi Action Serum, clinically proven to deliver a firmer feeling, visibly smoother face and neck,for younger looking skin in just 2 weeks.

Description

Youthful Vitality.

Discover No's Restore and Renew skincare range, now supercharged with our groundbreaking Restore & Renew Face and Neck Multi Action Serum. No7's first serum to deliver clinically proven results for both the face and neck.

Whilst laughter lines are a sign of a life well lived, as we age the exposed skin on both the face and neck becomes more fragil,less firm and has a more uneven texture.

Our Restore and Renew Skincare System works to address these key signs of ageing to help mature skinlook and feel like young skin again.

Formulated by No7, leaders in anti-ageing skincare.

Serum

Clinically proven to deliver 5 anti-ageing results: Face feels firmer, wrinkles are visbly reduced and skin tone is more even. Neck feels firmer and looks visibly smoother and less crepey.

Powered by our advanced anti-wrinkle, firming and lightening complexes plus a unique skin fortifying complex of calcium, amino acids and ceramides.

After the first application face and neck feel smoother. After 1 week face and neck look more radiant and feel firmer. After 2 weeks face and neck look younger, revitalised and lifted.

No7 Serums are designed to be used underneath your moisturiser to deliver key benefits directly to the skin.

Day Cream

Formulated with the protective power of Sunscreen Broad Spectrum SPF 15 to help give your skin protection from the No 1 cause of visible skin ageing.

Created to provide day long hydration and help boost your skin's repair and recovery processes, strengthening its resilience to future dryness. Our skin firming complex,containing a unique plant extract derived from the Persimmon Tree,works to boost your skin's vitlaity so that it behaves like younger skin.

The result is smoother, plumper looking skin that feels firmer and has a renewed healthy glow.

It is the perfect daytime partner to our Restore and Renew Face and Neck Multi Action Serum.

Night Cream

Nourish and revitalise your skin with this replenishing night time formula. Created to replenish lost lipids and help boost the skin's moisture barrier to rejuvenate the look of your skin overnight.

Works to help boost your skin's resilience to environmental stress,while our skin firming complex, containing a unique plant extract derived from the Persimmon Tree, works to boost your skin's vitality so that it behaves like younger skin.

The result is smoother, plumper looking skin that feels firmer.

It is the perfect night-time partner to our Restore and Renew Face and Neck Multi Action Serum.

For Best Results: After cleansing, smooth No7 Restore and Renew Face and Neck Multi Action Serum onto your face and neck until fully absorbed. In the morning, follow with the No7 Restore and Renew Day Cream. At night, follow with No7 Restore and Renew Night Cream.